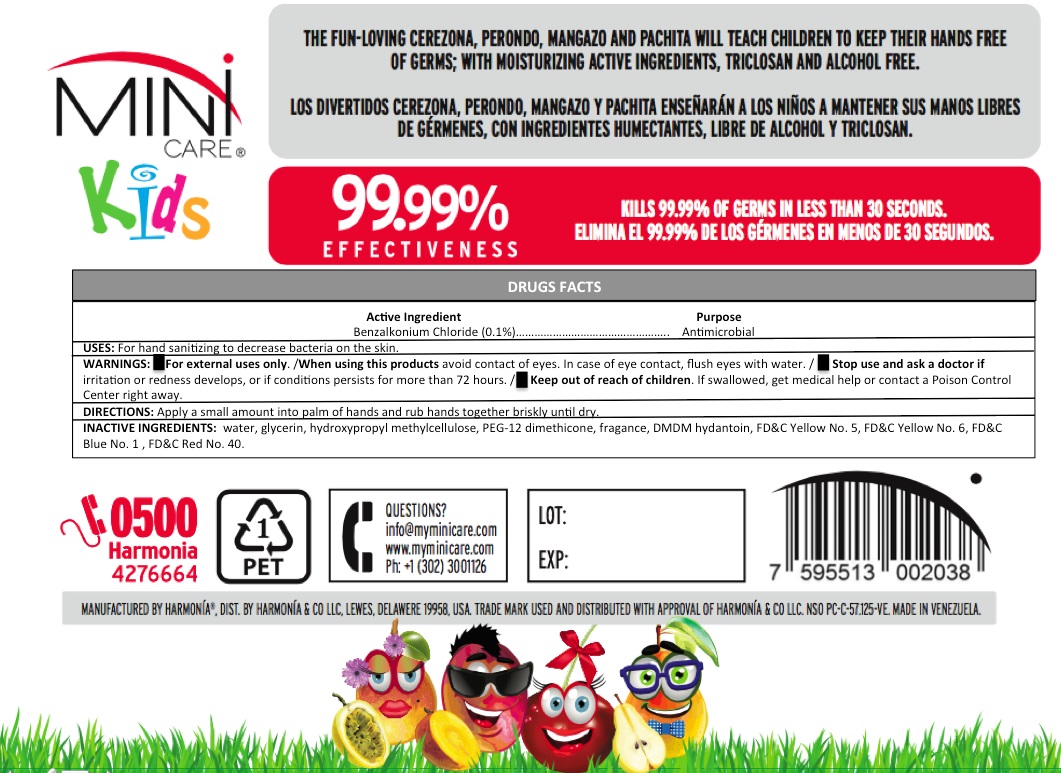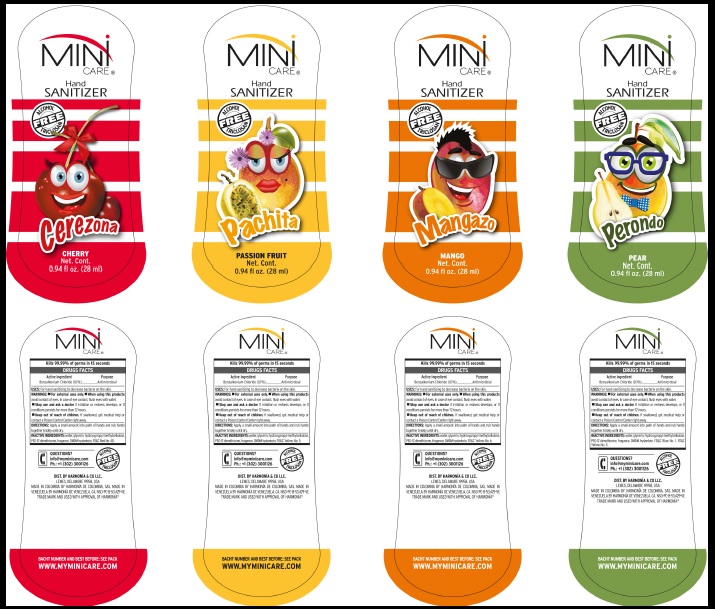 DRUG LABEL: Hand Sanitizer Kids
NDC: 73360-002 | Form: GEL
Manufacturer: Harmonia de Venezuela CA
Category: otc | Type: HUMAN OTC DRUG LABEL
Date: 20221230

ACTIVE INGREDIENTS: BENZALKONIUM CHLORIDE 1 mg/1 mL
INACTIVE INGREDIENTS: FD&C YELLOW NO. 5; FD&C BLUE NO. 1; FD&C YELLOW NO. 6; FD&C RED NO. 40; WATER; GLYCERIN; HYPROMELLOSE, UNSPECIFIED; PEG-12 DIMETHICONE (300 CST); DMDM HYDANTOIN

Drug Facts

Active Ingredient Purpose

Benzalkonium Chloride (0.1 %)--------------------- Antimicrobial

Uses

For hand sanitizing to decrease bacteria on the skin.

Warnings

For external uses only. / When using this products avoid contact of eyes. In case of eye contact, flush eyes with water. / Stop use and ask a doctor if irritation or redness develops, or if conditions persists for more than 72 hours. /Keep out of reach of children. If swallowed, get medical help or contact a Poison Control Center right away.

Directions

Apply a small amount into palm of hands and rub hands together briskly until dry.

Inactive Ingredients

water, glycerin, hydroxypropyl methylcellulose, PEG-12 dimethicone, fragance, DMDM hydantoin, FD&C Yellow No.5, FD&C Yellow No. 6, FD&C
Blue No. 1 , FD&C Red No. 40.